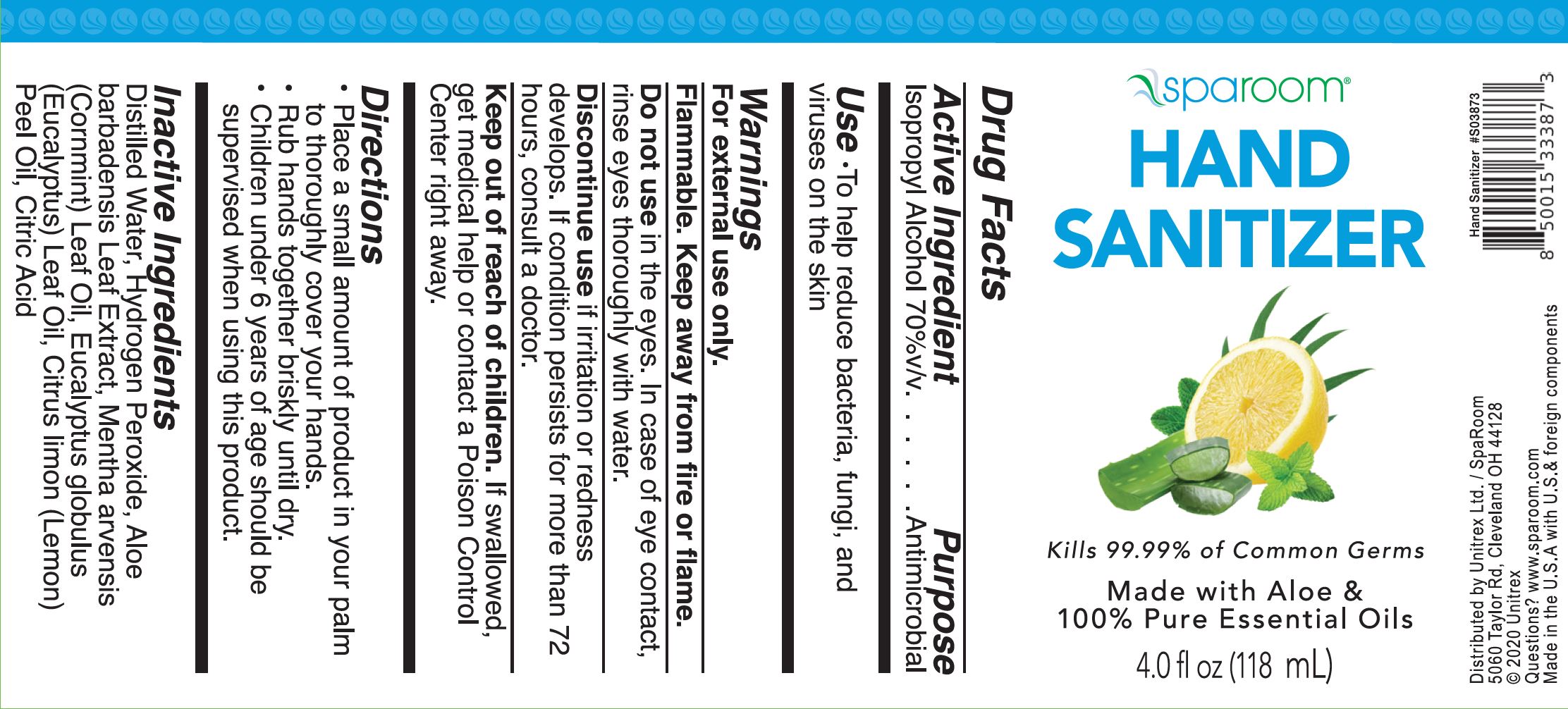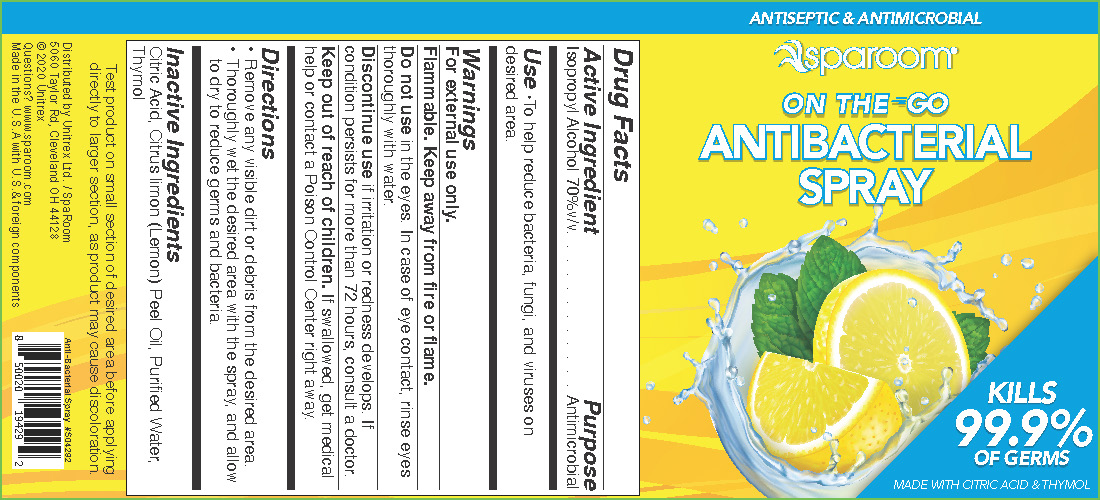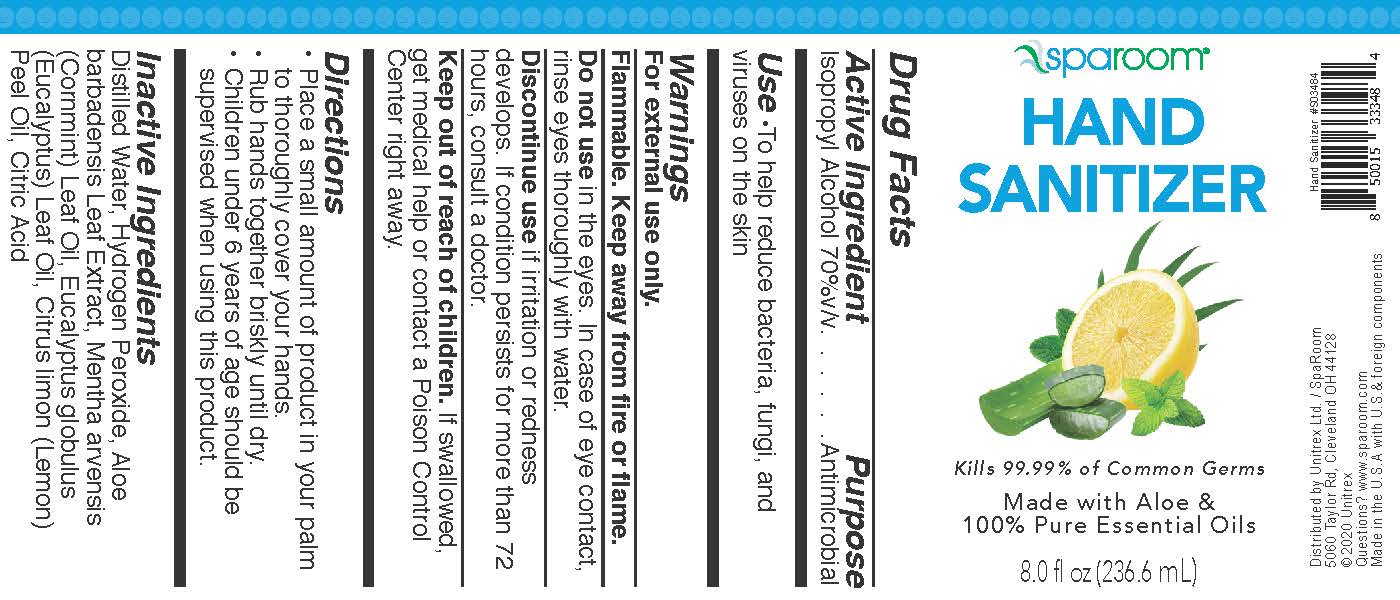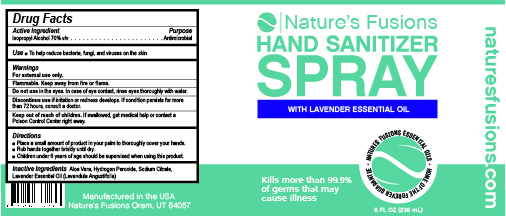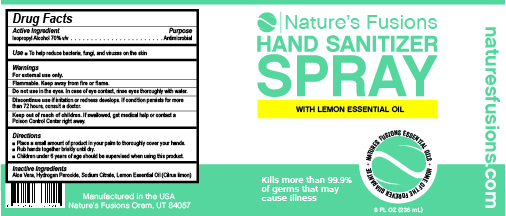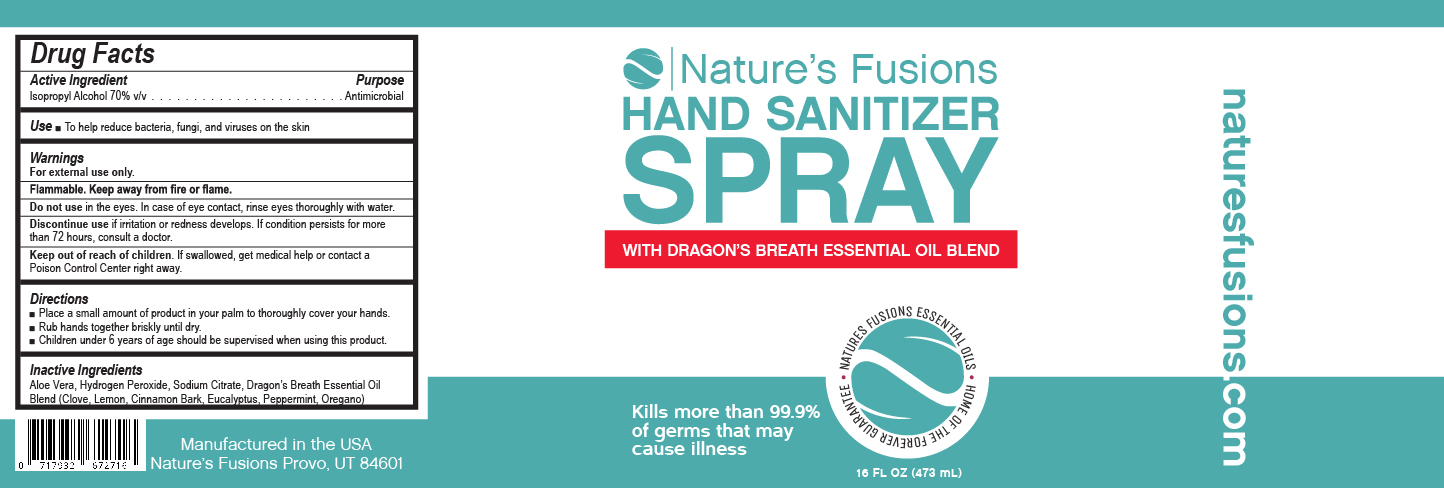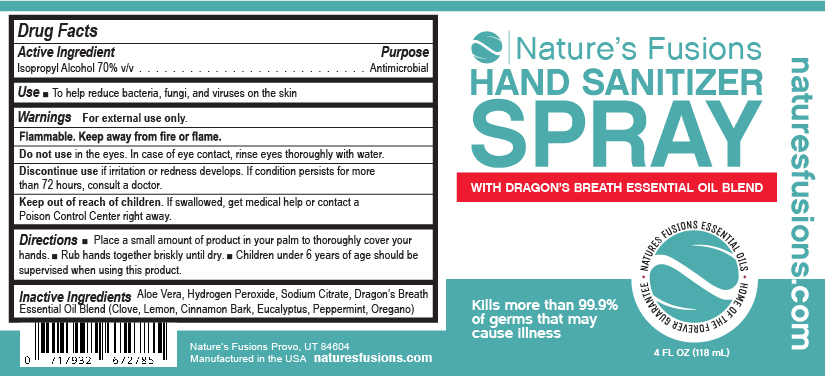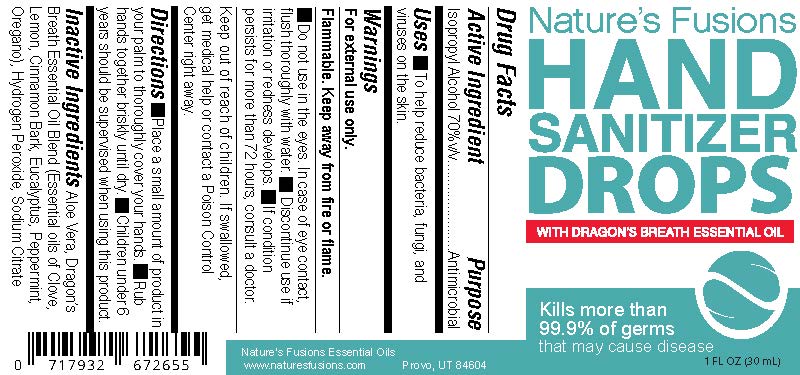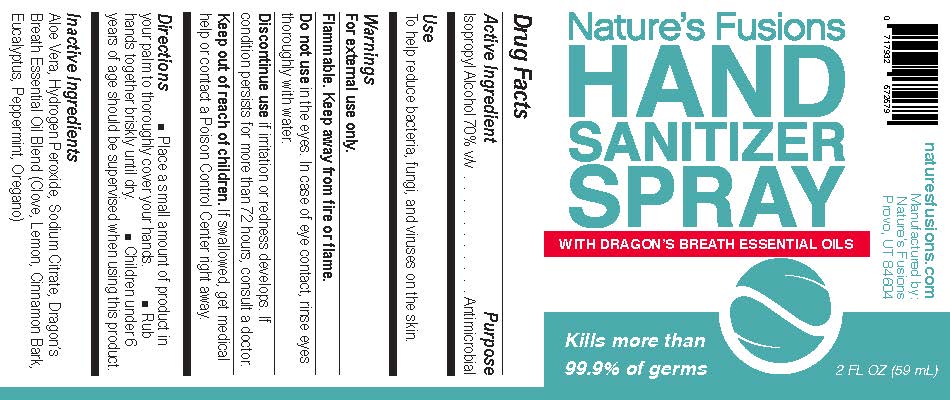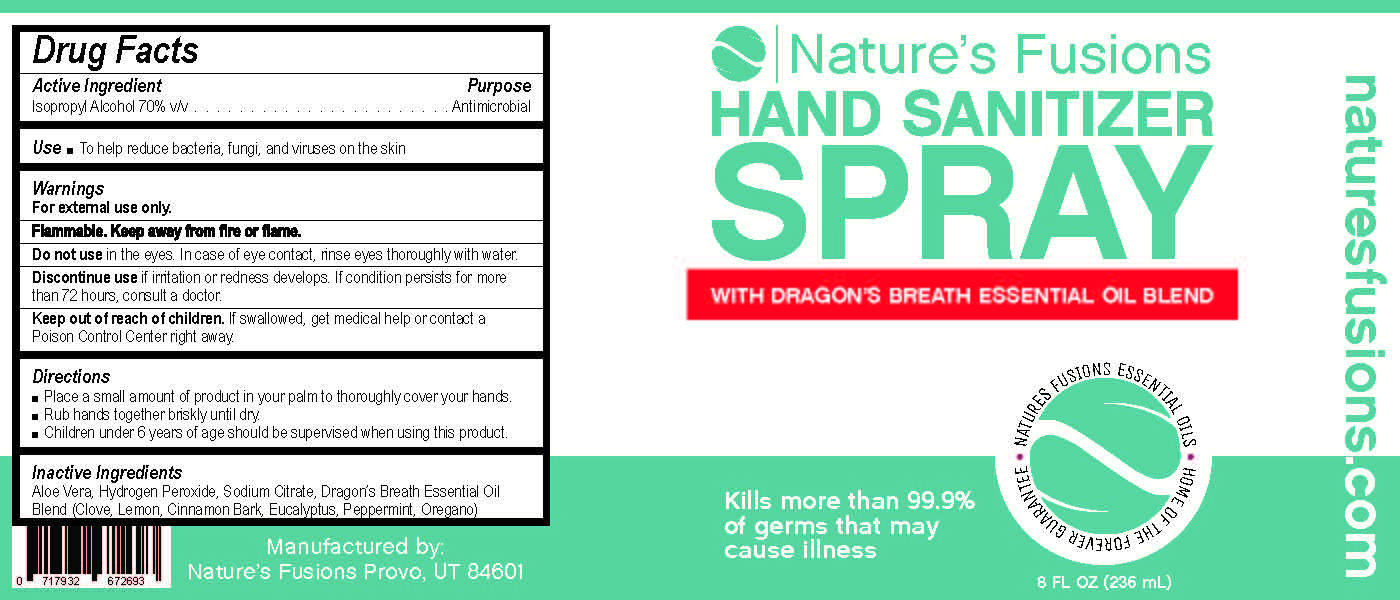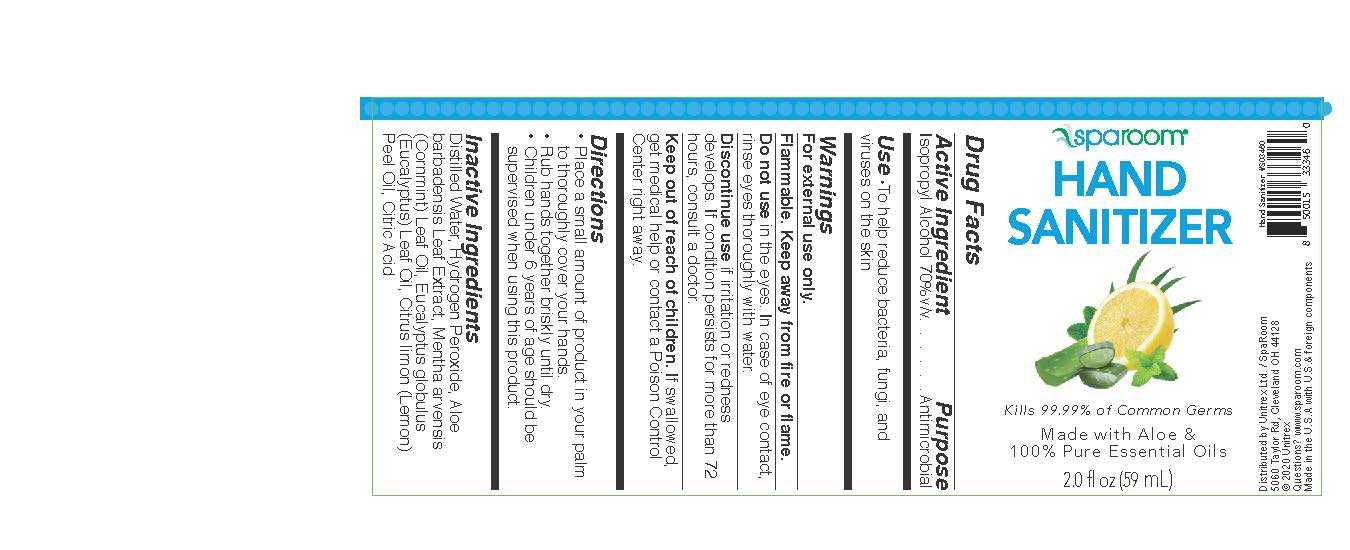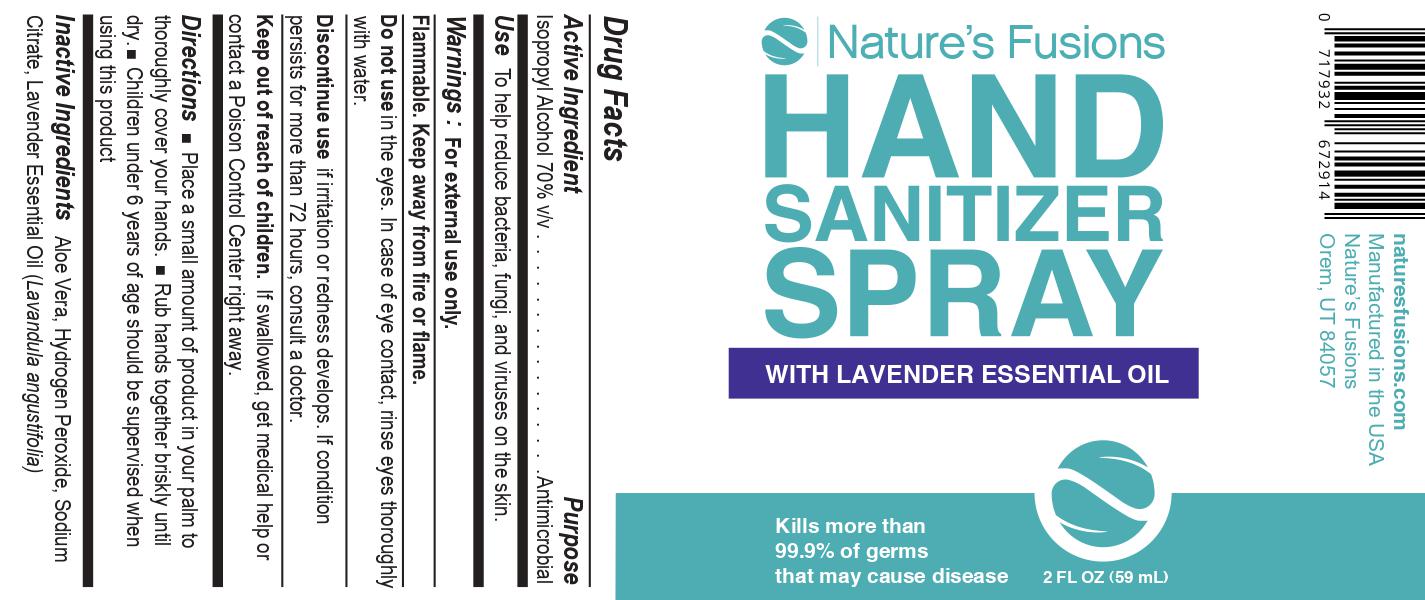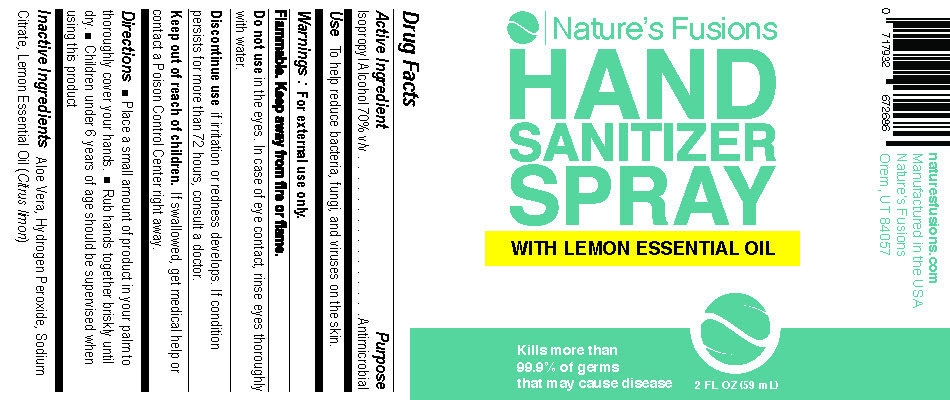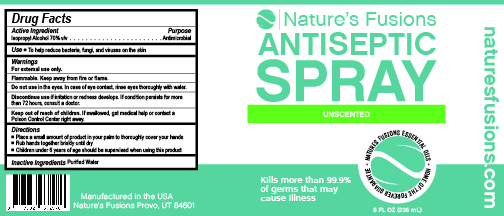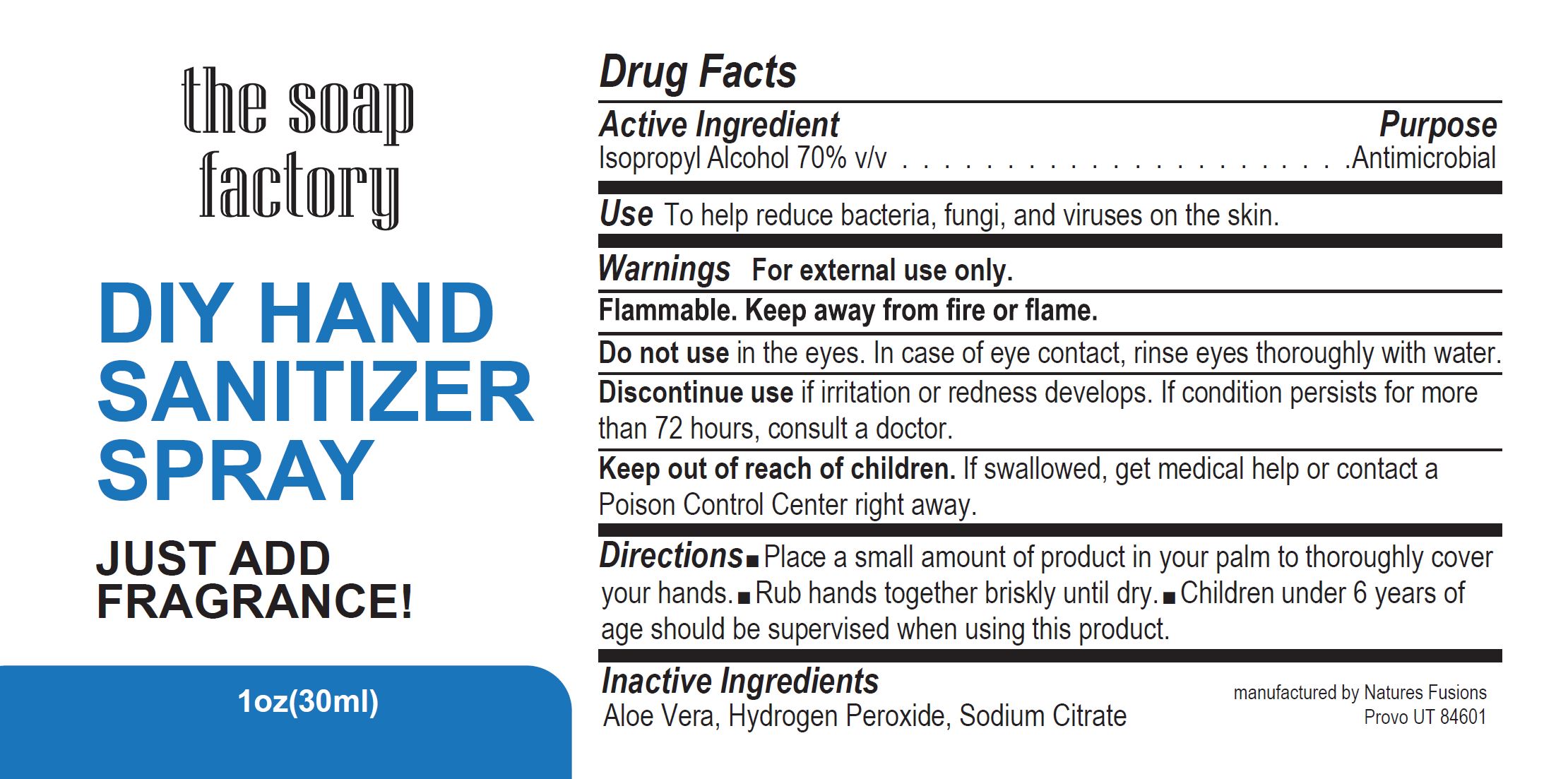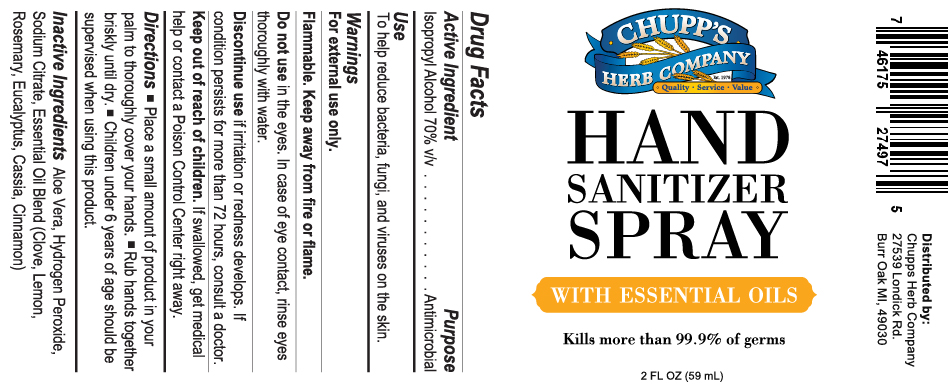 DRUG LABEL: Hand Sanitizer Liquid with Lavender
NDC: 73769-004 | Form: LIQUID
Manufacturer: NATURE'S FUSIONS, LLC
Category: otc | Type: HUMAN OTC DRUG LABEL
Date: 20240531

ACTIVE INGREDIENTS: ISOPROPYL ALCOHOL 70 mL/100 mL
INACTIVE INGREDIENTS: ALOE VERA LEAF; ANHYDROUS CITRIC ACID; SODIUM PERCARBONATE; LAVENDER OIL

Hand Sanitizer Liquids

PURPOSE

To help reduce bacteria, fungi, and viruses on the skin.

ACTIVE INGREDIENT

Isopropyl Alcohol 70% v/v - Antimicrobial

Keep out of reach of children. If swallowed, get medical help or contact a Poison Control Center right away.

INDICATIONS AND USAGE

- Place a small amount of product in your palm to thoroughly cover your hands.
- Rub hands together briskly until dry.
- Children under 6 years should be supervised when using this product.

INACTIVE INGREDIENT

Aloe Vera, Dragon's Breath Essential Oil Blend (Essential oils of Clove, Lemon, Cinnamon Bark, Eucalyptus, Peppermint, Oregano), Hydrogen Peroxide, Sodium Citrate

DOSAGE AND ADMINISTRATION

Place a small amount of product in your palm

WARNINGS

- For external use only.
- Flammable.
- Keep away from fire or flame.
- Do not use in eyes. In case of eye contact, flush thoroughly with water.
- Discontinue use if irritation or redness develops.
- If condition persists for more than 72 hours, consult a doctor.

PACKAGE LABEL

Antiseptic Spray

antiseptic spray 0